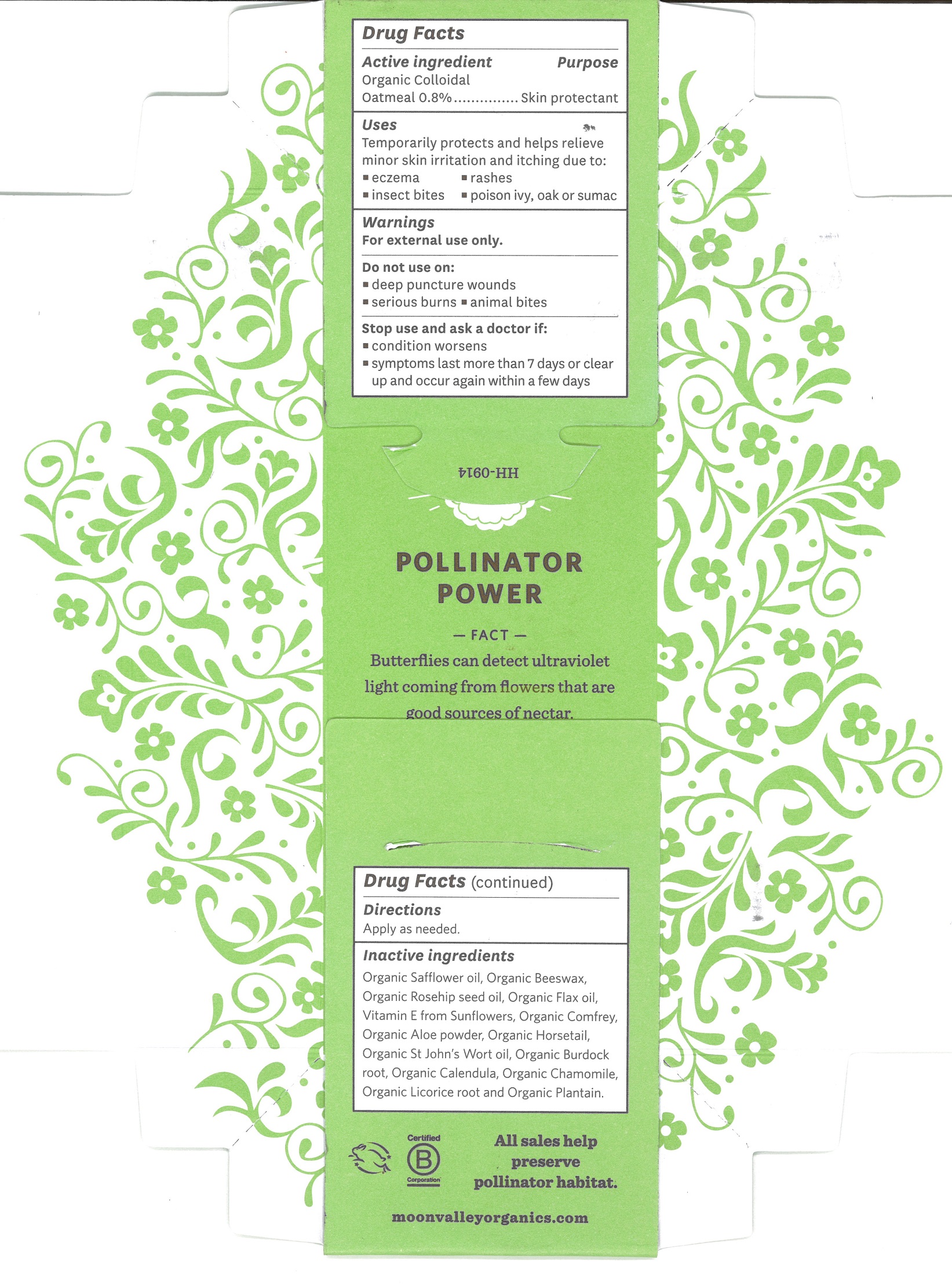 DRUG LABEL: EczaCalm
NDC: 65112-250 | Form: OINTMENT
Manufacturer: I Shay Cosmetics Inc
Category: otc | Type: HUMAN OTC DRUG LABEL
Date: 20241008

ACTIVE INGREDIENTS: OATMEAL 0.008 g/1 g
INACTIVE INGREDIENTS: SAFFLOWER OIL 0.67 g/1 g

EczaCalm Cream

ACTIVE INGREDIENT

Organic Colloidal Oatmeal 0.8% ... Skin Protectant

PURPOSE

Skin Protectant

WARNING: Keep out of reach of children.

INDICATIONS AND USAGE

Temporarily protects and helps relieve minor skin irritation and itching due to:

Eczema, rashes, insect bites, poison ivy, oak or sumac

INACTIVE INGREDIENT

Organic Safflower Oil, Organic Beeswax, Organic Rosehip Seed Oil, Organic Flax Oil, Vitamin E From Sunflowers, Organic Horsetail, Organic Comfrey, Organic Horsetail, Organic Aloe, Organic Calendula, Organic Burdock, Organic Licorice Root, Organic Chamomile, Organic St. John’s Wort, Organic Plantain.

WARNINGS

For external use only.

Do not use on:
deep puncture wounds
serious burns
animal bites

Stop use and ask a doctor if:
condition worsens
symptoms last more than 7 days or clear up and occur again within a few days

DOSAGE AND ADMINISTRATION

Apply as needed

PACKAGE LABEL

drug panel